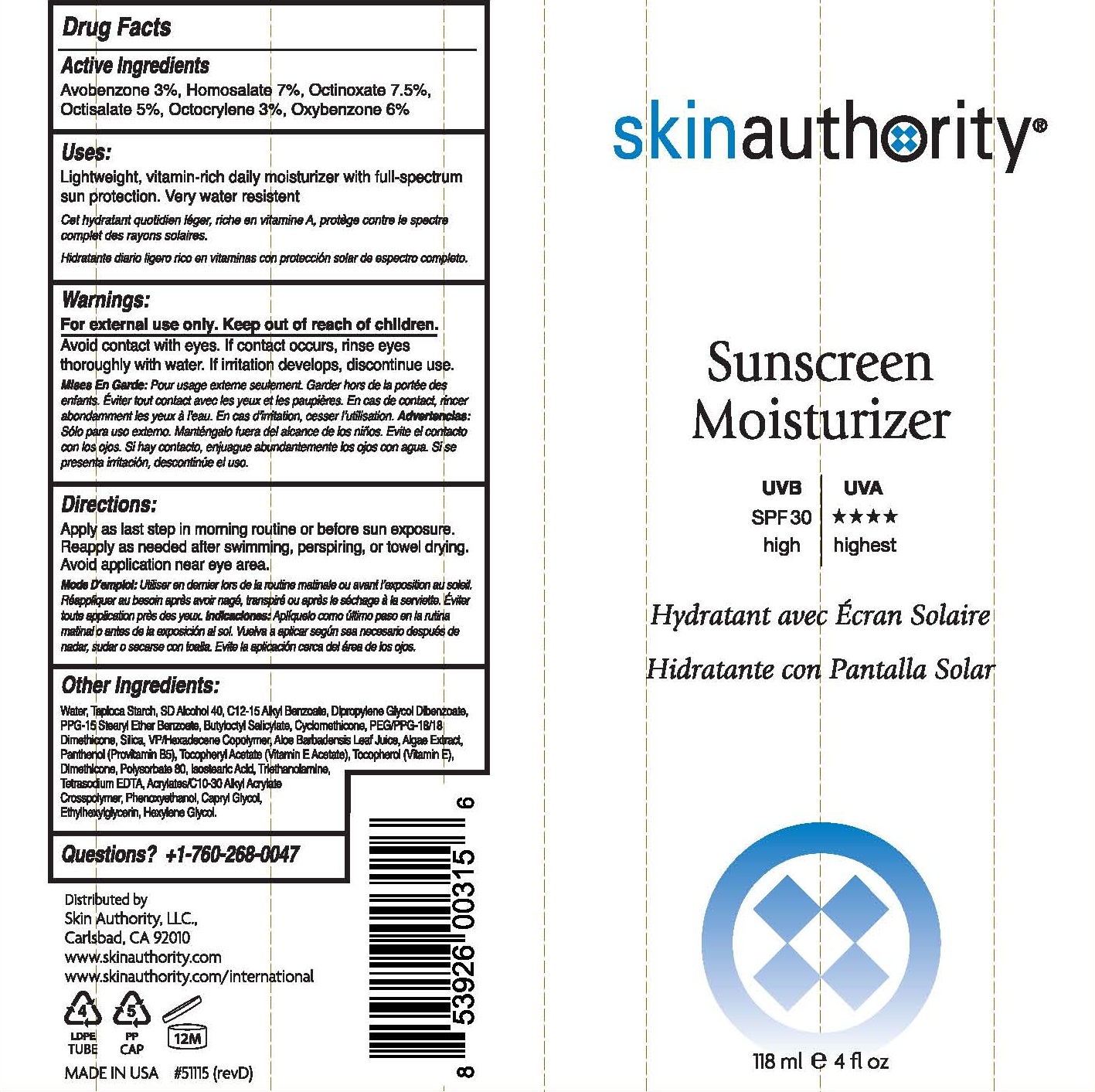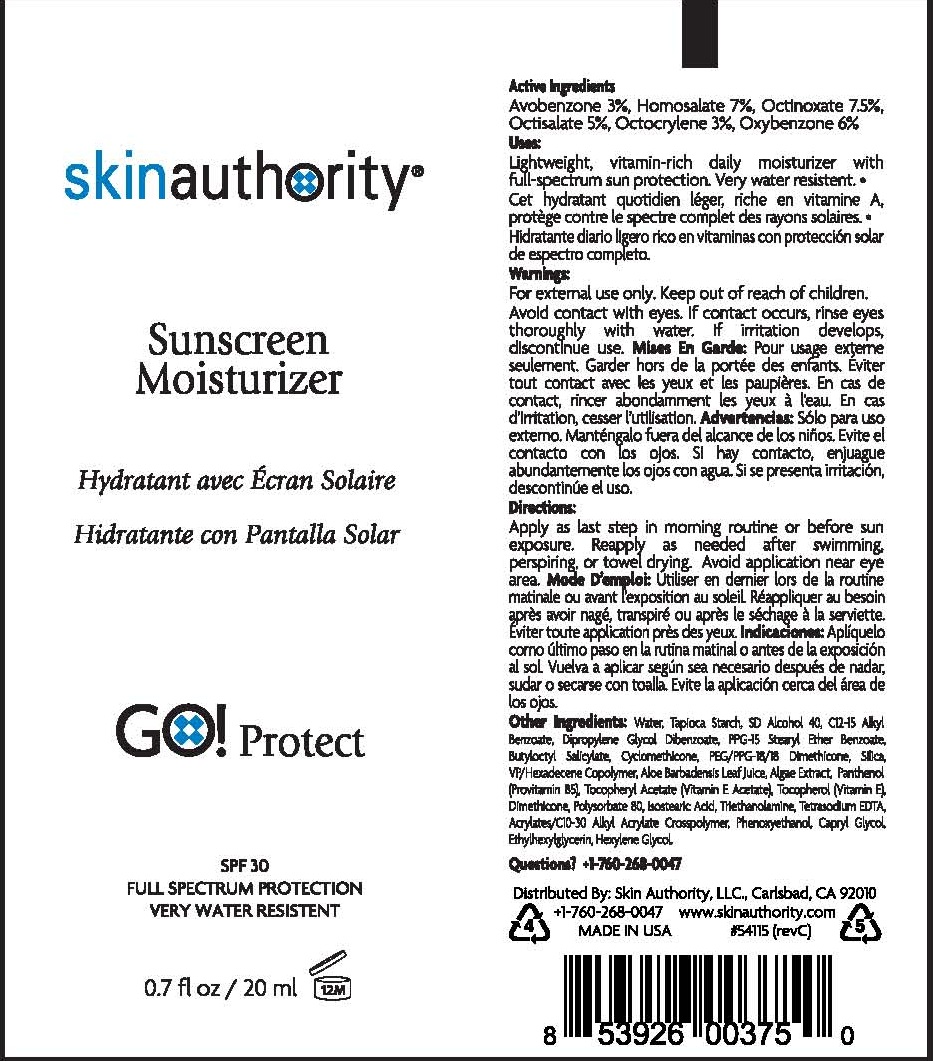 DRUG LABEL: SUNSCREEN MOISTURIZER
NDC: 46007-203 | Form: LOTION
Manufacturer: Skin Authority LLC
Category: otc | Type: HUMAN OTC DRUG LABEL
Date: 20251218

ACTIVE INGREDIENTS: AVOBENZONE 3 g/100 mL; OCTINOXATE 7.5 g/100 mL; OCTISALATE 5 g/100 mL; OXYBENZONE 6 g/100 mL; HOMOSALATE 7 g/100 mL; OCTOCRYLENE 3 g/100 mL
INACTIVE INGREDIENTS: WATER; STARCH, TAPIOCA; ALCOHOL; ALKYL (C12-15) BENZOATE; DIPROPYLENE GLYCOL DIBENZOATE; PPG-15 STEARYL ETHER BENZOATE; BUTYLOCTYL SALICYLATE; CYCLOMETHICONE; PEG/PPG-18/18 DIMETHICONE; SILICON DIOXIDE; COPOVIDONE K25-31; ALOE VERA LEAF; FUCUS VESICULOSUS; PANTHENOL; ALPHA-TOCOPHEROL ACETATE; TOCOPHEROL; DIMETHICONE; POLYSORBATE 80; ISOSTEARIC ACID; TROLAMINE; EDETATE SODIUM; CARBOMER INTERPOLYMER TYPE A (ALLYL SUCROSE CROSSLINKED); PHENOXYETHANOL; CAPRYLYL GLYCOL; ETHYLHEXYLGLYCERIN; HEXYLENE GLYCOL

Skin Authority - SUNSCREEN MOISTURIZER (46007-203)- delist

ACTIVE INGREDIENTS:

AVOBENZONE 3%, HOMOSALATE 7%, OCTINOXATE 7.5%, OCTISALATE 5%, OCTOCRYLENE 3%, OXYBENZONE 6%

PURPOSE:

SUNSCREEN

USES:

LIGHTWEIGHT, VITAMIN-RICH DAILY MOISTURIZER WITH FULL-SPECTRUM SUN PROTECTION. VERY WATER RESISTENT.

WARNINGS:

FOR EXTERNAL USE ONLY.

KEEP OUT OF REACH OF CHILDREN.

OTHER SAFETY INFORMATION

AVOID CONTACT WITH EYES. IF CONTACT OCCURS, RINSE EYES THOROUGHLY WITH WATER.

IF IRRITATION DEVELOPS, DISCONTINUE USE.

DIRECTIONS:

APPLY AS LAST STEP IN MORNING ROUTINE OR BEFORE SUN EXPOSURE. REAPPLY AS NEEDED AFTER SWIMMING, PERSPIRING, OR TOWEL DRYING. AVOID APPLICATION NEAR EYE AREA.

INACTIVE INGREDIENT

WATER, TAPIOCA STARCH, SD ALCOHOL 40, C12-15 ALKYL BENZOATE, DIPROPYLENE GLYCOL DIBENZOATE, PPG-15 STEARYL ETHER BENZOATE, BUTYLOCTYL SALICYLATE, CYCLOMETHICONE, PEG/PPG-18/18 DIMETHICONE, SILICA, VP/HEXADECENE COPOLYMER, ALOE BARBADENSIS LEAF JUICE, ALGAE EXTRACT, PANTHENOL, TOCOPHERYL ACETATE, TOCOPHEROL, DIMETHICONE, POLYSORBATE 80, ISOSTEARIC ACID, TRIETHANOLAMINE, TETRASODIUM EDTA, ACRYLATES/C10-30 ALKYL ACRYLATE CROSSPOLYMER, PHENOXYETHANOL, CAPRYL GLYCOL, ETHYLHEXYLGLYCERIN, HEXYLENE GLYCOL.

QUESTIONS? +1-760-268-0047

PACKAGE LABEL

SKIN AUTHORITY

SUNSCREEN MOISTURIZER

118 ML / 4 FL OZ